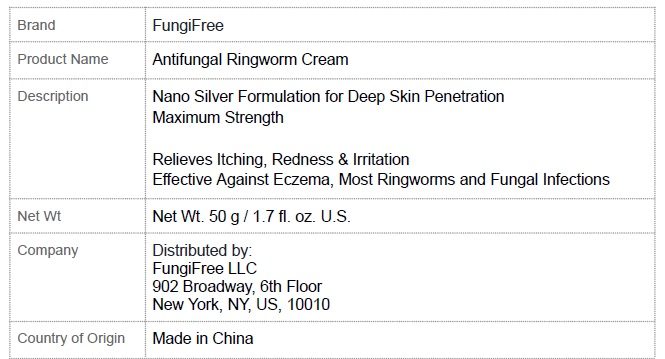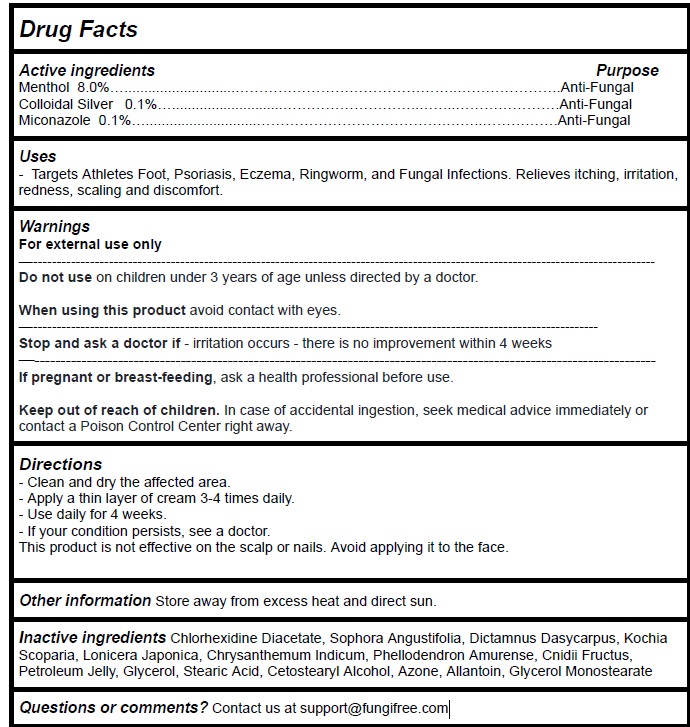 DRUG LABEL: FungiFree Antifungal Ringworm Cream
NDC: 83364-003 | Form: CREAM
Manufacturer: YITONGBADA (SHENZHEN) INTERNATIONAL TRADE CO., LTD
Category: otc | Type: HUMAN OTC DRUG LABEL
Date: 20240315

ACTIVE INGREDIENTS: MENTHOL, UNSPECIFIED FORM 8 g/100 g; SILVER 0.1 g/100 g; MICONAZOLE 0.1 g/100 g
INACTIVE INGREDIENTS: CHLORHEXIDINE ACETATE; SOPHORA FLAVESCENS ROOT; DICTAMNUS DASYCARPUS ROOT; BASSIA SCOPARIA WHOLE; LONICERA JAPONICA STEM; CHRYSANTHEMUM INDICUM FLOWER; PHELLODENDRON AMURENSE BARK; CNIDIUM MONNIERI FRUIT; PETROLATUM; GLYCERIN; STEARIC ACID; CETOSTEARYL ALCOHOL; LAUROCAPRAM; ALLANTOIN; GLYCERYL MONOSTEARATE

Active Ingredient Purpose

Menthol 8.0%…............................…………………..………………….Anti-Fungal
Colloidal Silver 0.1%…............................……..…..………………….Anti-Fungal
Miconazole 0.1%…............................…………….……..…………….Anti-Fungal

Uses

Targets Athletes Foot, Psoriasis, Eczema, Ringworm, and Fungal Infections. Relieves itching, irritation, redness, scaling and discomfort.

Warnings

For external use only
Do not use onchildren under 3 years of age unless directed by a doctor.

When using this productavoid contact with eyes.
Stop and ask a doctor if- irritation occurs - there is no improvement within 4 weeks
If pregnant or breast-feeding, ask a health professional before use.

Keep out of reach of children. In case of accidental ingestion, seek medical advice immediately or contact a Poison Control Center right away.

Directions

- Clean and dry the affected area.
- Apply a thin layer of cream 3-4 times daily.
- Use daily for 4 weeks.
- If your condition persists, see a doctor.
- This product is not effective on the scalp or nails. Avoid applying it to the face.

Other information

Store away from excess heat and direct sun.

Inactive ingredients

Chlorhexidine Diacetate, Sophora Angustifolia, Dictamnus Dasycarpus, Kochia Scoparia, Lonicera Japonica, Chrysanthemum Indicum, Phellodendron Amurense, Cnidii Fructus, Petroleum Jelly, Glycerol, Stearic Acid, Cetostearyl Alcohol, Azone, Allantoin, Glycerol Monostearate

Questions or comments?

Contact us at support@fungifree.com